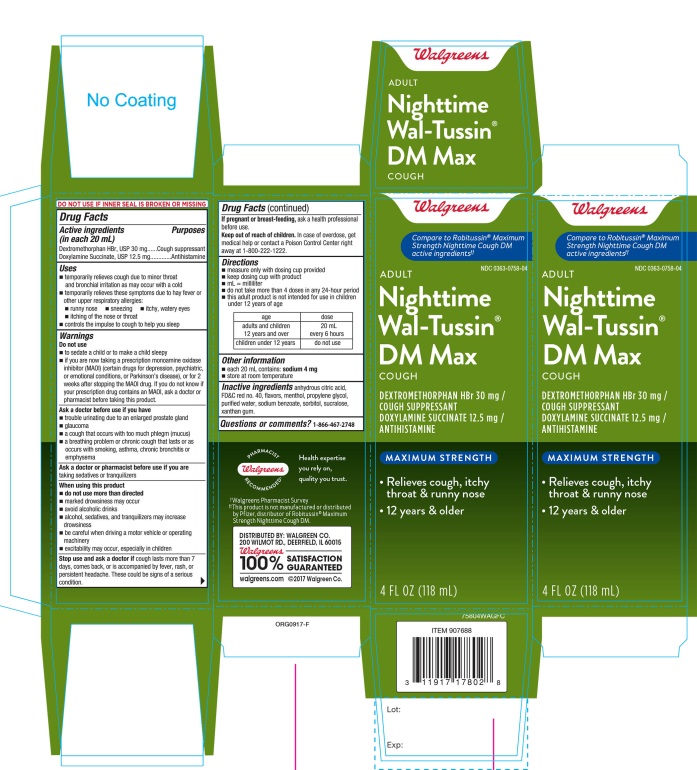 DRUG LABEL: Walgreens Adult Nighttime Wal Tussin DM Max Maximum Strength
NDC: 0363-0758 | Form: SOLUTION
Manufacturer: WALGREEN CO.
Category: otc | Type: HUMAN OTC DRUG LABEL
Date: 20170907

ACTIVE INGREDIENTS: DEXTROMETHORPHAN HYDROBROMIDE 30 mg/20 mL; DOXYLAMINE SUCCINATE 12.5 mg/20 mL
INACTIVE INGREDIENTS: ANHYDROUS CITRIC ACID; FD&C RED NO. 40; MENTHOL; PROPYLENE GLYCOL; WATER; SODIUM BENZOATE; SORBITOL; SUCRALOSE; XANTHAN GUM

Walgreens Adult Nighttime Wal-Tussin® DM Max Cough Maximum Strength

Active ingredients (in each 20 mL)

Dextromethorphan HBr ,USP 30 mg

Doxylamine Succinate, USP 12.5 mg

Purposes

Cough suppressant

Antihistamine

Uses

- temporarily relieves cough due to minor throat and bronchial irritation

as may occur with a cold.

- temporarily relieves these symptoms due to hay fever or other upper respiratory allergies:
- runny nose
- sneezing
- itchy, watery eyes
- itching of the nose or throat
- controls the impulse to cough to help you sleep

Warnings

Do not use

- to sedate a child or to make a child sleepy
- if you are now taking a prescription monoamine oxidase inhibitor (MAOI) (certain drugs for depression, psychiatric, or emotional conditions, or Parkinson’s disease), or for 2 weeks after stopping the MAOI drug. If you do not know if your prescription drug contains an MAOI, ask a doctor or pharmacist before taking this product.

Ask a doctor before use if you have

- trouble urinating due to an enlarged prostate gland
- glaucoma
- a cough that occurs with too much phlegm (mucus)
- a breathing problem or chronic cough that lasts or as occurs with smoking, asthma, chronic bronchitis or emphysema

Ask a doctor or pharmacist before use if you are

taking sedatives or tranquilizers

When using this product do not use more than directed

- do not use more than directed
- marked drowsiness may occur
- avoid alcoholic drinks
- alcohol, sedatives, and tranquilizers may increase drowsiness
- be careful when driving a motor vehicle or operating machinery
- excitability may occur, especially in children

Stop use and ask a doctor if

cough lasts more than 7 days, comes back, or is accompanied by fever, rash, or persistent headache. These could be signs of a serious condition.

If pregnant or breast-feeding,

ask a health professional before use.

Keep out of reach of children.

In case of overdose, get medical help or contact a Poison Control Center right away at 1-800-222-1222.

Directions

- measure only with dosing cup provided
- keep dosing cup with product
- mL= milliliter.
- do not take more than 4 doses in any 24-hour period.
- this adult product is not intended for use in children under 12 years of age.

age | dose
adults and children 12 years and over | 20 mL every 6 hours
children under 12 years | do not use

Other information:

- each 20mL contains: sodium 4 mg
- store at room temperature

Inactive ingredients

anhydrous citric acid, FD&C red no. 40, flavors, menthol, propylene glycol, purified water, sodium benzoate, sorbitol, sucralose, xanthan gum.

Questions or comments?

1-866-467-2748

DO NOT USE IF INNER SEAL IS BROKEN OR MISSING

Principal Display Panel

Walgreens

Compare to Robitussin® Maximum Strength Nighttime Cough DM active ingredients‡

NDC 0363-0758-04

ADULT

Nighttime

Wal-Tussin®

DM Max

COUGH

DEXTROMETHORPHAN HBr 30 mg / COUGH SUPPRESSANT

DOXYLAMINE SUCCINATE 12.5 mg / ANTIHISTAMINE

MAXIMUM STRENGTH

- Relieves cough, itchy throat & runny nose
- 12 Years & older

‡Walgreens Pharmacist Survey

WALGREENS PHARMACIST RECOMMENDED‡

‡‡This product is not manufactured or distributed by Pfizer distributor of Robitussin® Maximum Strength Nighttime Cough DM

DISTRIBUTED BY: WALGREEN CO.

200 WILMOT RD.,DEERFIELD,IL 60015

Walgreens 100% SATISFACTION GUARANTEED

Walgreens.com ©2017 Walgreen Co.

4 FL OZ (118 mL)